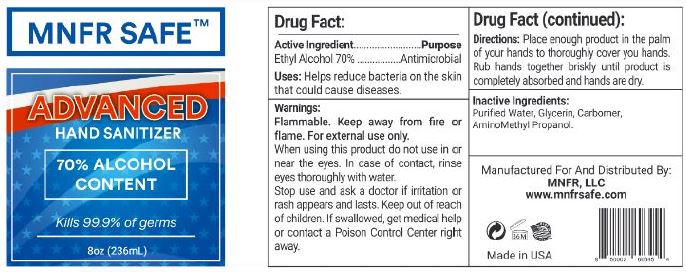 DRUG LABEL: MNFR SAFE
NDC: 61577-1115 | Form: GEL
Manufacturer: SOMBRA COSMETICS
Category: otc | Type: HUMAN OTC DRUG LABEL
Date: 20200622

ACTIVE INGREDIENTS: ALCOHOL 70 mL/100 mL
INACTIVE INGREDIENTS: WATER; GLYCERIN; CARBOMER HOMOPOLYMER TYPE C; AMINOMETHYLPROPANOL

MNFR SAFE Advanced Hand Sanitizer

Active Ingredients

Ethyl Alcohol 70%

Purpose

Antiseptic, Hand Sanitizer

Uses

Helps reduce bacteria on the skin that could cause diseases.

Warnings

Flammable. Keep fire or flame. For external use only.

Do not use

When using this product, do not use in or near the eyes. In case of contact, rinse eyes thoroughly with water.

When using this product, do not use in or near the eyes. In case of contact, rinse eyes thoroughly with water.

Stop use and ask a doctor if irritation or rash appears and lasts.

Keep out of reach of children. If swallowed, get medical help or contact a Poison Control Center right away.

Directions

Place enough product in the palm of your hands to thoroughly cover your hands. Rub hands together briskly until product is completely absorbed and hands are dry.

Other information

- Store between 15-30C (59-86F)
  Avoid freezing and excessive heat above 40C (105F)

Inactive ingredients

glycerin, purified water, carbomer, aminomethyl propanol